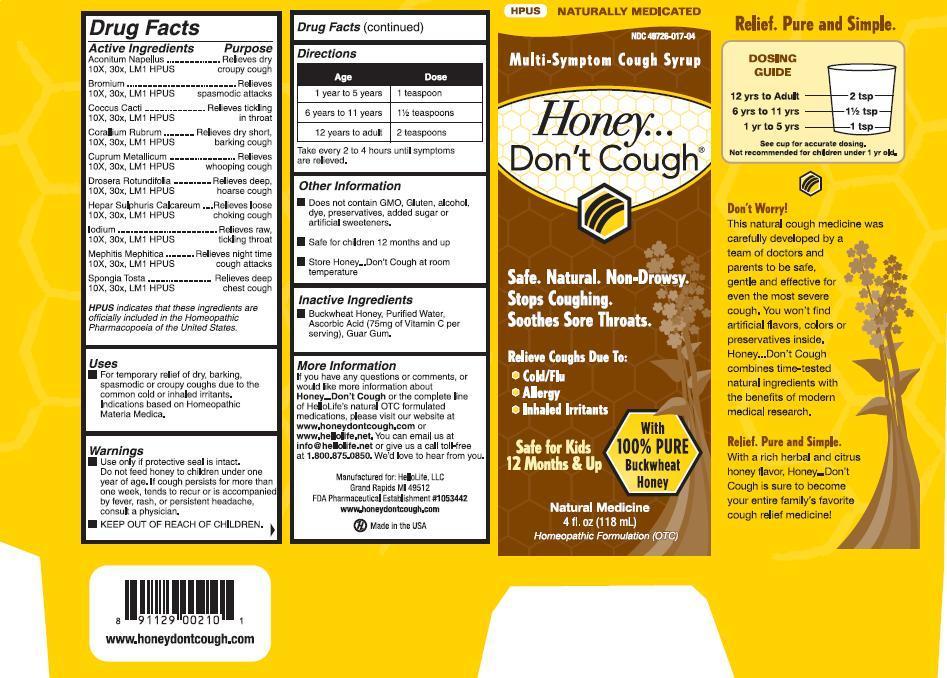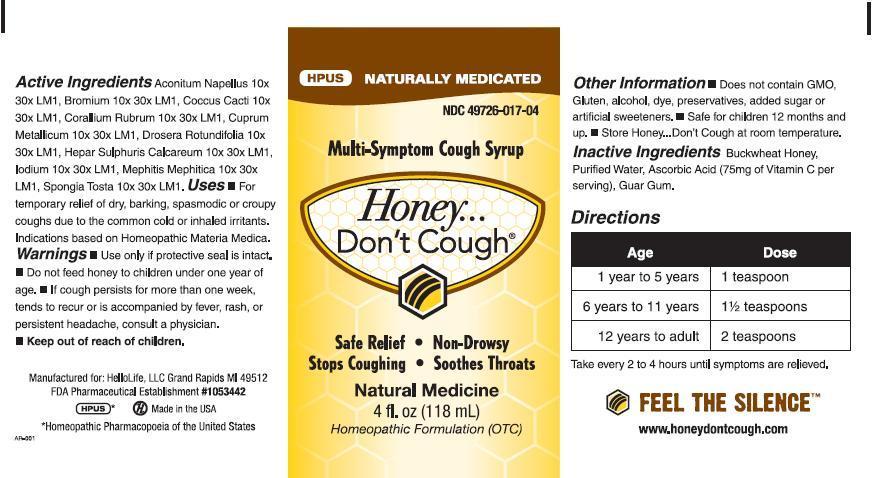 DRUG LABEL: Honey Dont Cough
NDC: 49726-017 | Form: SYRUP
Manufacturer: Hello Life Inc.
Category: homeopathic | Type: HUMAN OTC DRUG LABEL
Date: 20181226

ACTIVE INGREDIENTS: ACONITUM NAPELLUS 10 [hp_X]/118 mL; MEPHITIS MEPHITIS ANAL GLAND FLUID 10 [hp_X]/118 mL; BROMINE 10 [hp_X]/118 mL; PROTORTONIA CACTI 10 [hp_X]/118 mL; CORALLIUM RUBRUM EXOSKELETON 10 [hp_X]/118 mL; COPPER 10 [hp_X]/118 mL; DROSERA ROTUNDIFOLIA 10 [hp_X]/118 mL; CALCIUM SULFIDE 10 [hp_X]/118 mL; IODINE 10 [hp_X]/118 mL; SPONGIA OFFICINALIS SKELETON, ROASTED 10 [hp_X]/118 mL
INACTIVE INGREDIENTS: ASCORBIC ACID; GUAR GUM

Active Ingredients:

Acontium Napellus 10X, 30x, LM1 HPUS, Bromium 10X, 30x, LM1 HPUS, Coccus Cacti 10X, 30x, LM1 HPUS, Corallium Rubrum 10X, 30x, LM1 HPUS, Cuprum Metallicum 10X, 30x, LM1 HPUS, Drosera Rotundifolia 10X, 30x, LM1 HPUS, Hepar Sulphuris Calcareum 10X, 30x, LM1 HPUS, Iodium 10X, 30x, LM1 HPUS, Mephitis Mephitica 10X, 30x, LM1 HPUS, Spongia Tosta 10X, 30x, LM1 HPUS

HPUS indicates that these ingredients are officially included in the Homeopathic Pharmacopoeia of the United States.

Purpose:

Acontium Napellus..................Relieves dry croupy cough

Bromium................................Relieves spasmodic attacks

Coccus Cacti..........................Relieves tickling in throat

Corallium Rubrum...................Relieves dry short barking cough

Cuprum Metallicum................Relieves whooping cough

Drosera Rotundifolia...............Relieves deep, hoarse cough

Hepar Sulphuris Calcareum.....Relieves loose choking cough

Iodium...................................Relieves raw, tickling throat

Mephitis Mephitica.................Relieves night time cough attacks

Spongia Tosta.......................Relieves deep chest cough

Uses:

For temporary relief of dry, barking, spasmodic or croupy coughs due to the common cold or inhaled irritants. Indications based on Homeopathic Materia Medica.

Warnings:

- Use only if protective seal is intact. Do not feed honey to children under one year of age. If cough persists for more than one week, tends to recur or is accompanied by fever, rash, or persistent headache, consult a physician.

- KEEP OUT OF THE REACH OF CHILDREN.

Directions:

Age Dose

1 years to 5 years 1 teaspoon

6 years to 11 years 1 1/2 teaspoons

12 years to adult 2 teaspoons

Take every 2 to 4 hours until symptoms are relieved.

Other Information:

- Does not contain GMO, Gluten, alcohol, dye, preservatives, added sugar or artificial sweetners.
- Safe for children 12 months and up
- Store Honey..Don't Cough at room temperature

INACTIVE INGREDIENT

- Buckwheat Honey, Purified Water, Ascorbic Acid (75mg of Vitamin C per serving), Guar Gum.

More Information:

If you have any questions or comments, or would like more information about Honey..Don't Cough or the complete line of HelloLife's natural OTC formulated medications, please visit our website at www.honeydontcough.com or www.hellolife.net. You can email us at info@hellolife.net or give us a call toll-fee at 1.800.875.0850. We'd love to hear from you.

Manufactured for: HelloLife, LLC
Grand Rapids MI 49512
FDA Pharmaceutical Establishment

#1053442

www.honeydontcough.com

Made in the USA

PACKAGE LABEL

With 100% PURE Buckwheat Honey
Natural Medicine
4 fl. oz (118 mL)
Homeopathic Formulation (OTC)